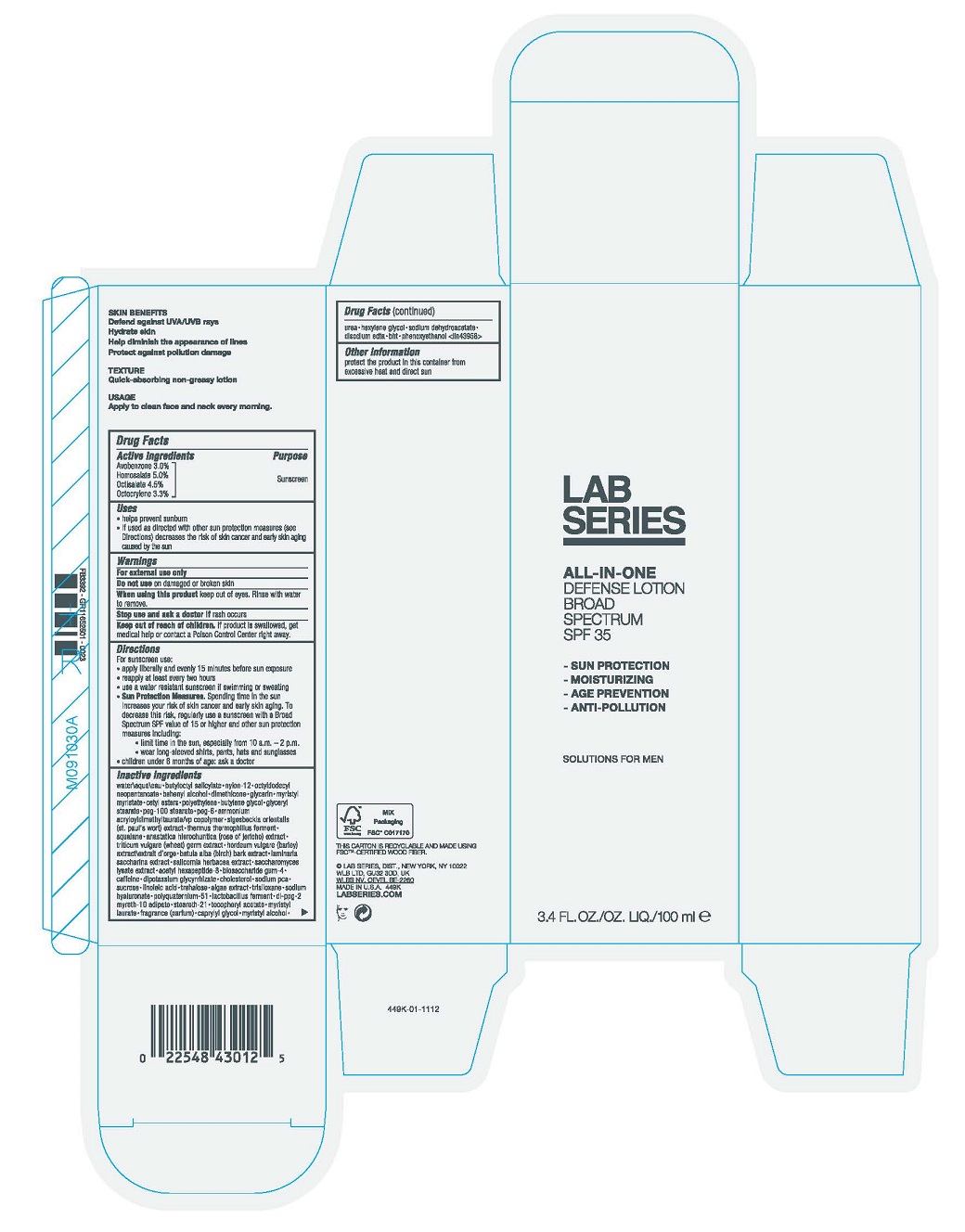 DRUG LABEL: LAB SERIES DAY RESCUE DEFENSE BROAD SPECTRUM SPF 35
NDC: 42472-010 | Form: LOTION
Manufacturer: Aramis Inc.
Category: otc | Type: HUMAN OTC DRUG LABEL
Date: 20241205

ACTIVE INGREDIENTS: AVOBENZONE 0.03 g/1 mL; HOMOSALATE 0.05 g/1 mL; OCTISALATE 0.045 g/1 mL; OXYBENZONE 0.033 g/1 mL
INACTIVE INGREDIENTS: CHOLESTEROL; SODIUM PYRROLIDONE CARBOXYLATE; SUCROSE; LINOLEIC ACID; TREHALOSE; WATER; BUTYLOCTYL SALICYLATE; NYLON-12; OCTYLDODECYL NEOPENTANOATE; DOCOSANOL; DIMETHICONE; GLYCERIN; MYRISTYL MYRISTATE; CETYL ESTERS WAX; HIGH DENSITY POLYETHYLENE; BUTYLENE GLYCOL; GLYCERYL MONOSTEARATE; PEG-100 STEARATE; POLYETHYLENE GLYCOL 300; AMMONIUM ACRYLOYLDIMETHYLTAURATE/VP COPOLYMER; THERMUS THERMOPHILUS LYSATE; SQUALANE; SELAGINELLA LEPIDOPHYLLA WHOLE; WHEAT; BARLEY; ACETYL HEXAPEPTIDE-8; BIOSACCHARIDE GUM-4; CAFFEINE; GLYCYRRHIZINATE DIPOTASSIUM; TRISILOXANE; HYALURONATE SODIUM; LIMOSILACTOBACILLUS REUTERI; DI-PPG-2 MYRETH-10 ADIPATE; STEARETH-21; MYRISTYL LAURATE; CAPRYLYL GLYCOL; MYRISTYL ALCOHOL; UREA; HEXYLENE GLYCOL; SODIUM DEHYDROACETATE; EDETATE DISODIUM ANHYDROUS; BUTYLATED HYDROXYTOLUENE; PHENOXYETHANOL

LAB SERIES DAY RESCUE DEFENSE LOTION BROAD SPECTRUM SPF 35

Drug Facts

ACTIVE INGREDIENT

Active Ingredients | Purpose
Avobenzone 3.0% | Sunscreen
Homosalate 5.0% | Sunscreen
Octisalate 4.5% | Sunscreen
Octocrylene 3.3% | Sunscreen

Uses

- Helps prevent sunburn
- If used as directed with other sun protection measures (see Directions), decreases the risk of skin cancer and early skin aging caused by the sun

Warnings

For external use only

Do not use on damaged or broken skin

When using this product keep out of eyes. Rinse with water to remove.

Stop use and ask a doctor if rash occurs

Keep out of reach of children. If product is swallowed, get medical help or contact a Poison Control Center right away.

Directions

- Apply liberally 15 minutes before sun exposure
- Reapply at least every two hours
- Use a water resistant sunscreen if swimming or sweating
- Sun Protection Measures. Spending time in the sun increases your risk of skin cancer and early skin aging. To decrease this risk, regularly use a sunscreen with a Broad Spectrum SPF value of 15 or higher and other sun protection measures including:
  - Limit time in the sun, especially from 10 a.m. – 2 p.m.
  - Wear long-sleeved shirts, pants, hats and sunglasses
- Children under 6 months of age: ask a doctor

Inactive Ingredients

WATER\AQUA\EAU ∙ BUTYLOCTYL SALICYLATE ∙ NYLON-12 ∙ OCTYLDODECYL NEOPENTANOATE ∙ BEHENYL ALCOHOL ∙ DIMETHICONE ∙ GLYCERIN ∙ MYRISTYL MYRISTATE ∙ CETYL ESTERS ∙ POLYETHYLENE ∙ BUTYLENE GLYCOL ∙ GLYCERYL STEARATE ∙ PEG-100 STEARATE ∙ PEG-6 ∙ AMMONIUM ACRYLOYLDIMETHYLTAURATE/VP COPOLYMER ∙ SIGESBECKIA ORIENTALIS (ST. PAUL'S WORT) EXTRACT ∙ THERMUS THERMOPHILLUS FERMENT ∙ SQUALANE ∙ ANASTATICA HIEROCHUNTICA (ROSE OF JERICHO) EXTRACT ∙ TRITICUM VULGARE (WHEAT) GERM EXTRACT ∙ HORDEUM VULGARE (BARLEY) EXTRACT\EXTRAIT D'ORGE ∙ BETULA ALBA (BIRCH) BARK EXTRACT ∙ LAMINARIA SACCHARINA EXTRACT ∙ SALICORNIA HERBACEA EXTRACT ∙ SACCHAROMYCES LYSATE EXTRACT ∙ ACETYL HEXAPEPTIDE-8 ∙ BIOSACCHARIDE GUM-4 ∙ CAFFEINE ∙ DIPOTASSIUM GLYCYRRHIZATE ∙ CHOLESTEROL ∙ SODIUM PCA ∙ SUCROSE ∙ LINOLEIC ACID ∙ TREHALOSE ∙ ALGAE EXTRACT ∙ TRISILOXANE ∙ SODIUM HYALURONATE ∙ POLYQUATERNIUM-51 ∙ LACTOBACILLUS FERMENT ∙ DI-PPG-2 MYRETH-10 ADIPATE ∙ STEARETH-21 ∙ TOCOPHERYL ACETATE∙ MYRISTYL LAURATE ∙ FRAGRANCE (PARFUM) ∙ CAPRYLYL GLYCOL ∙ MYRISTYL ALCOHOL ∙ UREA ∙ HEXYLENE GLYCOL ∙ SODIUM DEHYDROACETATE ∙ DISODIUM EDTA ∙ BHT ∙ PHENOXYETHANOL <ILN43958>

Other information

- Protect the product in this container from excessive heat and direct sun

PRINCIPAL DISPLAY PANEL - 100 ml Tube Carton

LAB
SERIES
ALL-IN-ONE

DEFENSE LOTION
BROAD SPECTRUM
SPF 35

3.4 FL. OZ.
100 ml e